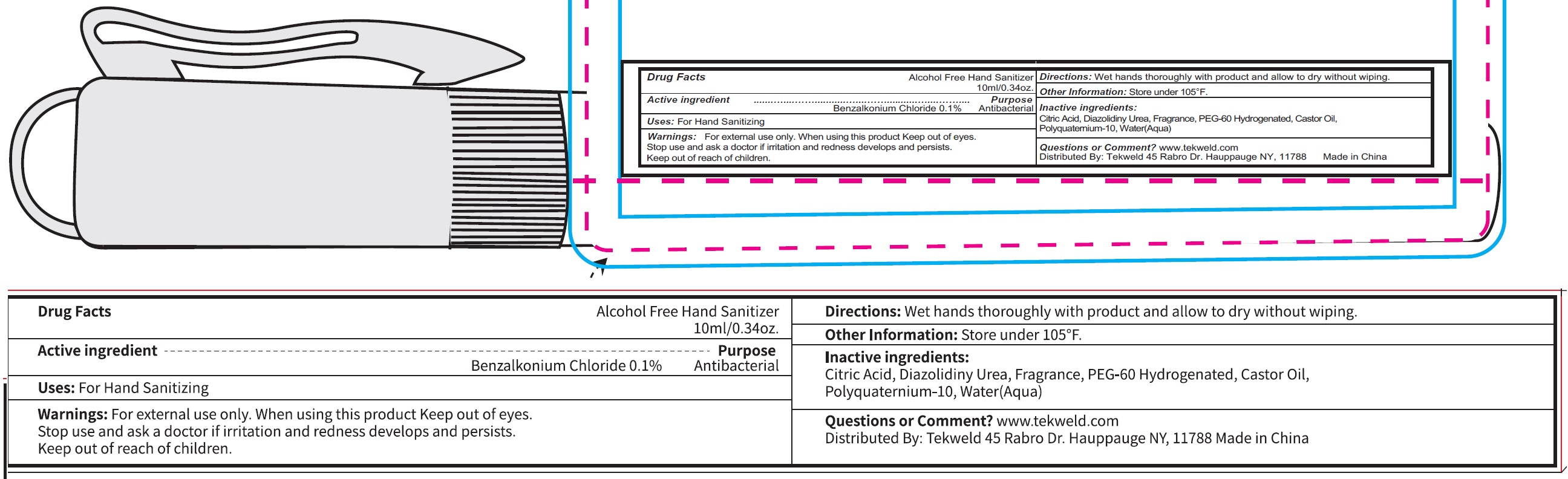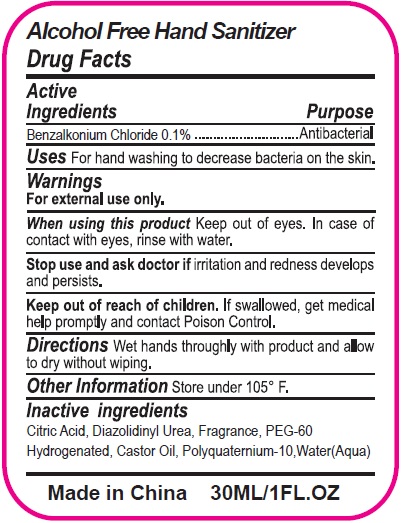 DRUG LABEL: Alcohol Free Hand Sanitizer
NDC: 70412-120 | Form: GEL
Manufacturer: Zhejiang Ayan Biotech Co.,Ltd.
Category: otc | Type: HUMAN OTC DRUG LABEL
Date: 20240227

ACTIVE INGREDIENTS: BENZALKONIUM CHLORIDE 1 mg/1 mL
INACTIVE INGREDIENTS: CITRIC ACID MONOHYDRATE; DIAZOLIDINYL UREA; CASTOR OIL; WATER

Alcohol Free Hand Sanitizer

Active ingredient

Benzalkonium Chloride 0.1 %

Purpose

Antibacterial

Uses:

For Hand Sanitizing

Warnings:

For external use only.

When using this product

Keep out of eyes.

Stop use and ask doctor if

irritation and redness develops and persists.

Directions:

Wet hands throughly with product and allow to dry without wiping.

Other Information:

Store under 105° F.

Inactive ingredients:

Citric Acid, Diazolidinyl Urea, Fragrance, PEG-60 Hydrogenated, Castor Oil, Polyquaternium-10,Water(Aqua)

Questions or Comment?

www.tekweld.com